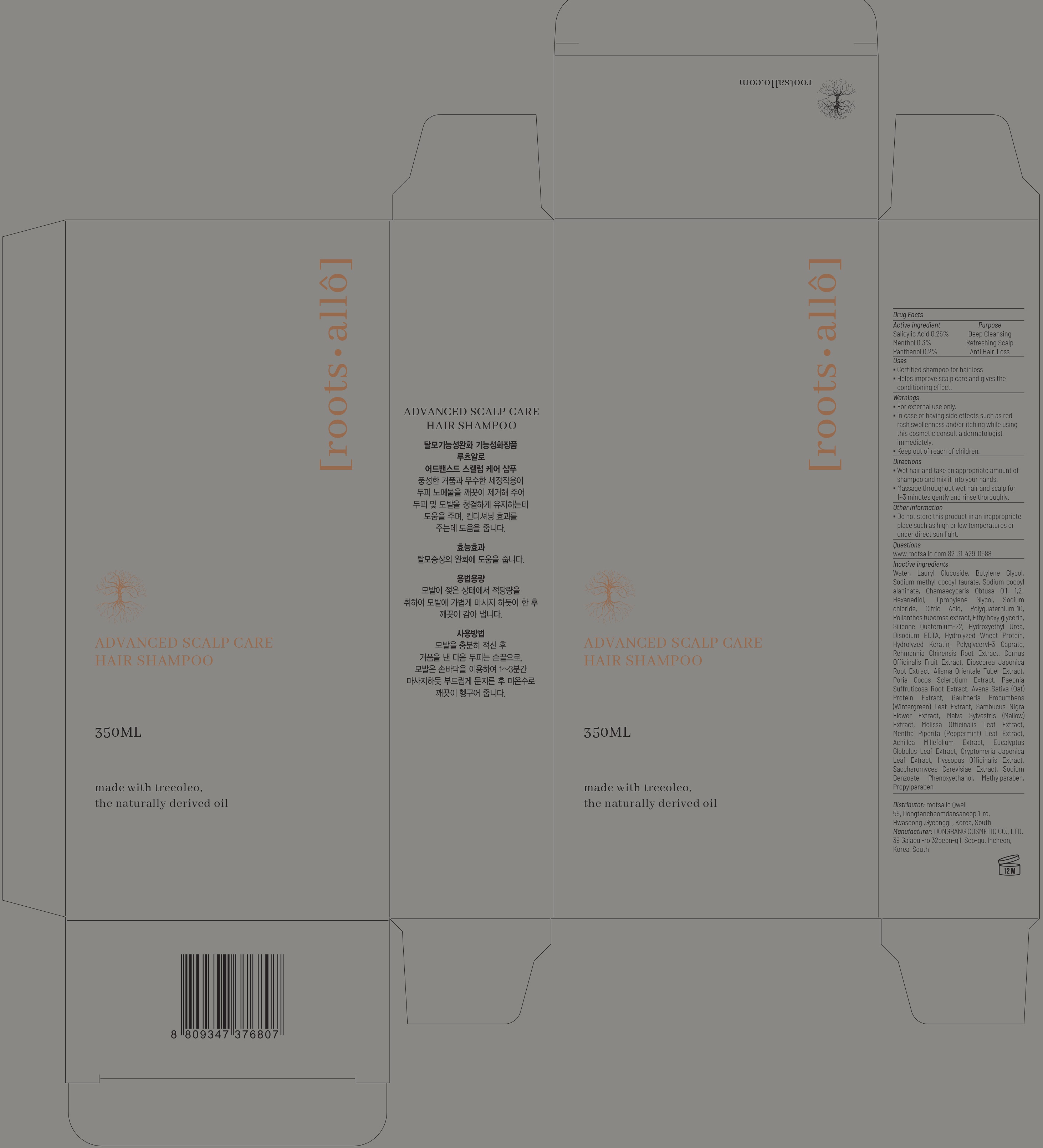 DRUG LABEL: ROOTSALLO ADVANCED SCALP CARE HAIR
NDC: 82450-040 | Form: SHAMPOO
Manufacturer: rootsallo Qwell
Category: otc | Type: HUMAN OTC DRUG LABEL
Date: 20211230

ACTIVE INGREDIENTS: Salicylic Acid 0.25 g/100 mL; Menthol 0.3 g/100 mL; Panthenol 0.2 g/100 mL
INACTIVE INGREDIENTS: Water; Lauryl Glucoside; Butylene Glycol

ACTIVE INGREDIENTS

Salicylic Acid 0.25%
Menthol 0.3%
Panthenol 0.2%

PURPOSE

Deep Cleansing, Refreshing Scalp, Anti Hair-Loss

Uses

Certified shampoo for hair loss
Helps improve scalp care and gives the conditioning effect.

Warnings

For external use only.
In case of having side effects such as red rash, swollenness and/or itching while using this cosmetic consult a dermatologist immediately.
Keep out of reach of children.

KEEP OUT OF REACH OF CHILDREN

Directions

Wet hair and take an appropriate amount of shampoo and mix it into your hands. Massage throughout wet hair and scalp for 1~3 minutes gently and rinse thoroughly.

Other Information

Do not store this product in an inappropriate place such as high or low temperatures or under direct sun light.

Questions

www.rootsallo.com 82-31-429-0588

Inactive ingredients

Water, Lauryl Glucoside, Butylene Glycol, Sodium methyl cocoyl taurate, Sodium cocoyl alaninate, Chamaecyparis Obtusa Oil, 1,2-Hexanediol, Dipropylene Glycol, Sodium chloride, Citric Acid, Polyquaternium-10, Polianthes tuberosa extract, Ethylhexylglycerin, Silicone Quaternium-22, Hydroxyethyl Urea, Disodium EDTA, Hydrolyzed Wheat Protein, Hydrolyzed Keratin, Polyglyceryl-3 Caprate, Rehmannia Chinensis Root Extract, Cornus Officinalis Fruit Extract, Dioscorea Japonica Root Extract, Alisma Orientale Tuber Extract, Poria Cocos Sclerotium Extract, Paeonia Suffruticosa Root Extract, Avena Sativa (Oat) Protein Extract, Gaultheria Procumbens (Wintergreen) Leaf Extract, Sambucus Nigra Flower Extract, Malva Sylvestris (Mallow) Extract, Melissa Officinalis Leaf Extract, Mentha Piperita (Peppermint) Leaf Extract, Achillea Millefolium Extract, Eucalyptus Globulus Leaf Extract, Cryptomeria Japonica Leaf Extract, Hyssopus Officinalis Extract, Saccharomyces Cerevisiae Extract, Sodium Benzoate, Phenoxyethanol, Methylparaben, Propylparaben